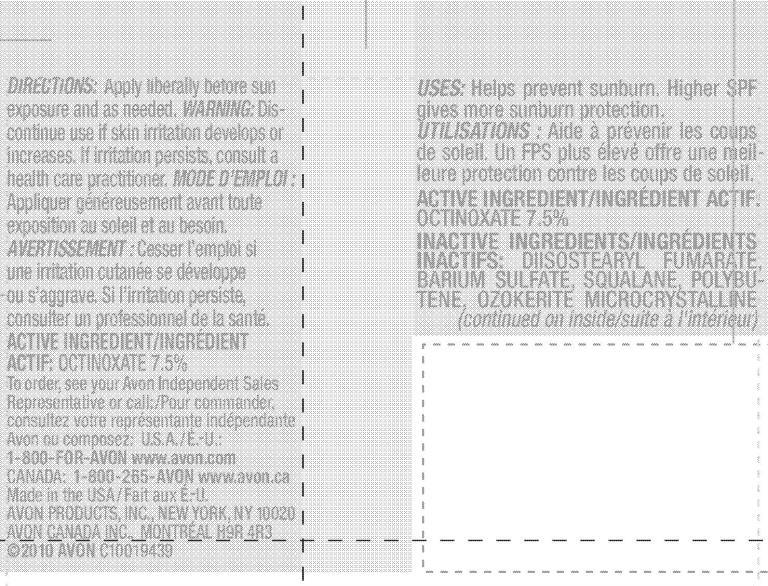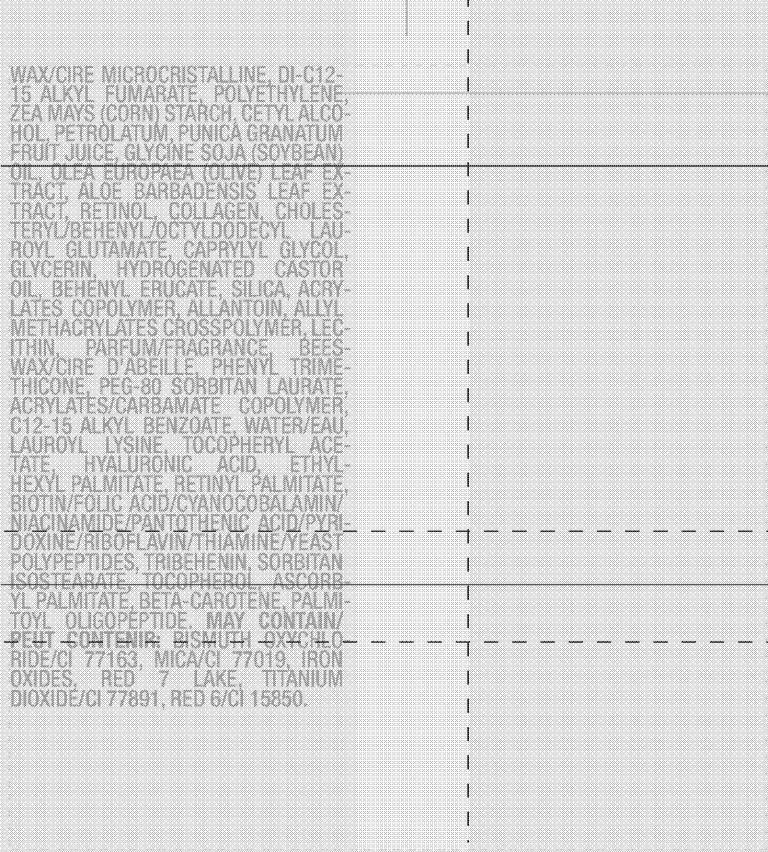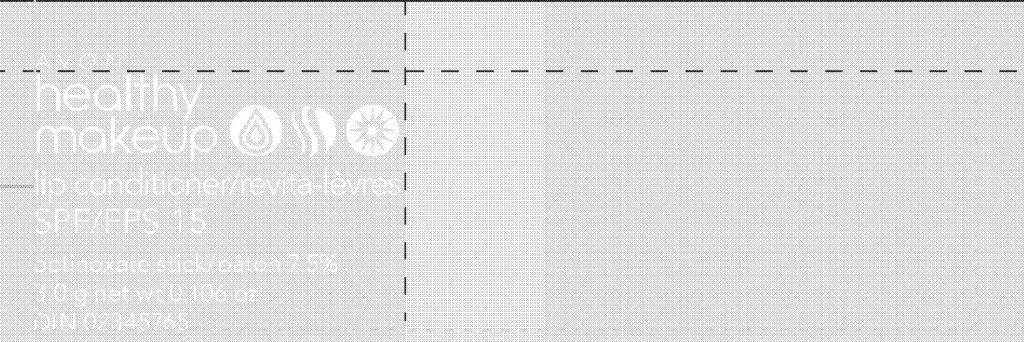 DRUG LABEL: Healthy Makeup
NDC: 10096-0215 | Form: LIPSTICK
Manufacturer: Avon Products, Inc.
Category: otc | Type: HUMAN OTC DRUG LABEL
Date: 20100610

ACTIVE INGREDIENTS: OCTINOXATE 225 mg/3 g
INACTIVE INGREDIENTS: BARIUM SULFATE; SQUALANE; CETYL ALCOHOL; PETROLATUM; RETINOL; CAPRYLYL GLYCOL; GLYCERIN; HYDROGENATED CASTOR OIL ; ALLANTOIN; PHENYL TRIMETHICONE; C12-15 ALKYL BENZOATE; WATER; HYALURONIC ACID; ETHYLHEXYL PALMITATE; ASCORBYL PALMITATE; BETA CAROTENE; BISMUTH OXYCHLORIDE; MICA; TITANIUM DIOXIDE

DOSAGE AND ADMINISTRATION

DIRECTIONS: Apply liberally before sun
exposure and as needed.

WARNINGS

WARNING: Discontinue use if skin irritation
develops or increases. If irritation
persists, consult a health care
practitioner.

ACTIVE INGREDIENT/INGREDIENT ACTIF:
OCTINOXATE 7.5%

INDICATIONS AND USAGE

USES: Helps prevent sunburn. Higher SPF
gives more sunburn protection.

INACTIVE INGREDIENTS/INGREDIENTS INACTIFS:
DIISOSTEARYL FUMARATE
BARIUM SULFATE
SQUALANE
POLYBUTENE
OZOKERITE
MICROCRYSTALLINE WAX/CIRE MICROCRISTALLINE
DI-C12-15 ALKYL FUMARATE
POLYETHYLENE
ZEA MAYS (CORN) STARCH
CETYL ALCOHOL
PETROLATUM
PUNICA GRANATUM FRUIT JUICE
GLYCINE SOJA (SOYBEAN) OIL
OLEA EUROPAEA (OLIVE) LEAF EXTRACT
ALOE BARBADENSIS LEAF EXTRACT
RETINOL
COLLAGEN
CHOLESTERYL/BEHENYL/OCTYLDODECYL LAUROYL GLUTAMATE
CAPRYLYL GLYCOL
GLYCERIN
HYDROGENATED CASTOR OIL
BEHENYL ERUCATE
SILICA
ACRYLATES COPOLYMER
ALLANTOIN
ALLYL METHACRYLATES CROSSPOLYMER
LECITHIN
PARFUM/FRAGRANCE
BEESWAX/CIRE D'ABEILLE
PHENYL TRIMETHICONE
PEG-80 SORBITAN LAURATE
ACRYLATES/CARBAMATE COPOLYMER
C12-15 ALKYL BENZOATE
WATER/EAU
LAUROYL LYSINE
TOCOPHERYL ACETATE
HYALURONIC ACID
ETHYLHEXYL PALMITATE
RETINYL PALMITATE
Biotin/Folic Acid/Cyanocobalamin/Niacinamide/Pantothenic Acid/Pyridoxine/Riboflavin/Thiamine/Yeast Polypeptides
TRIBEHENIN
SORBITAN ISOSTEARATE
TOCOPHEROL
ASCORBYL PALMITATE
BETA-CAROTENE
PALMITOYL OLIGOPEPTIDE
MAY CONTAIN:
BISMUTH OXYCHLORIDE/CI 77163
MICA/CI 77019
IRON OXIDES
RED 7 LAKE
TITANIUM DIOXIDE/CI 77891
RED 6/CI 15850